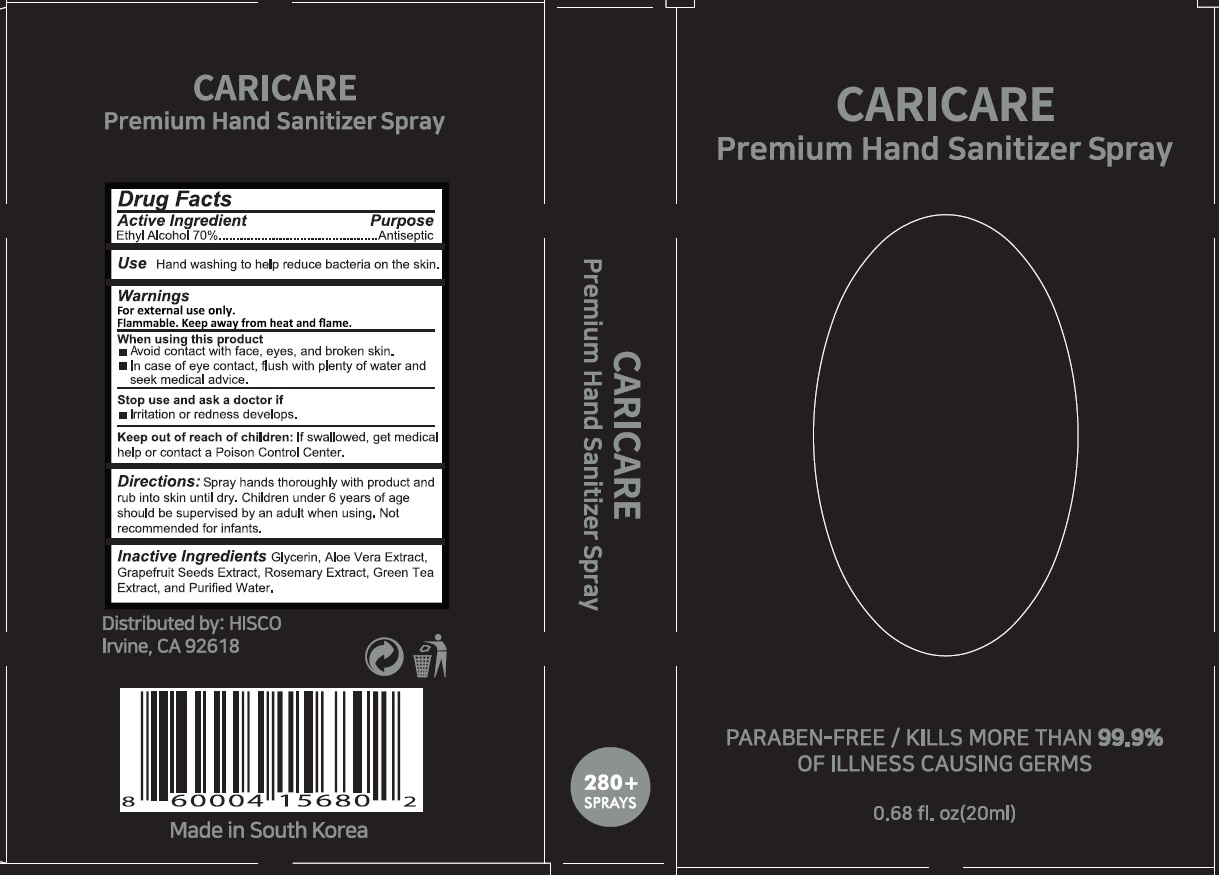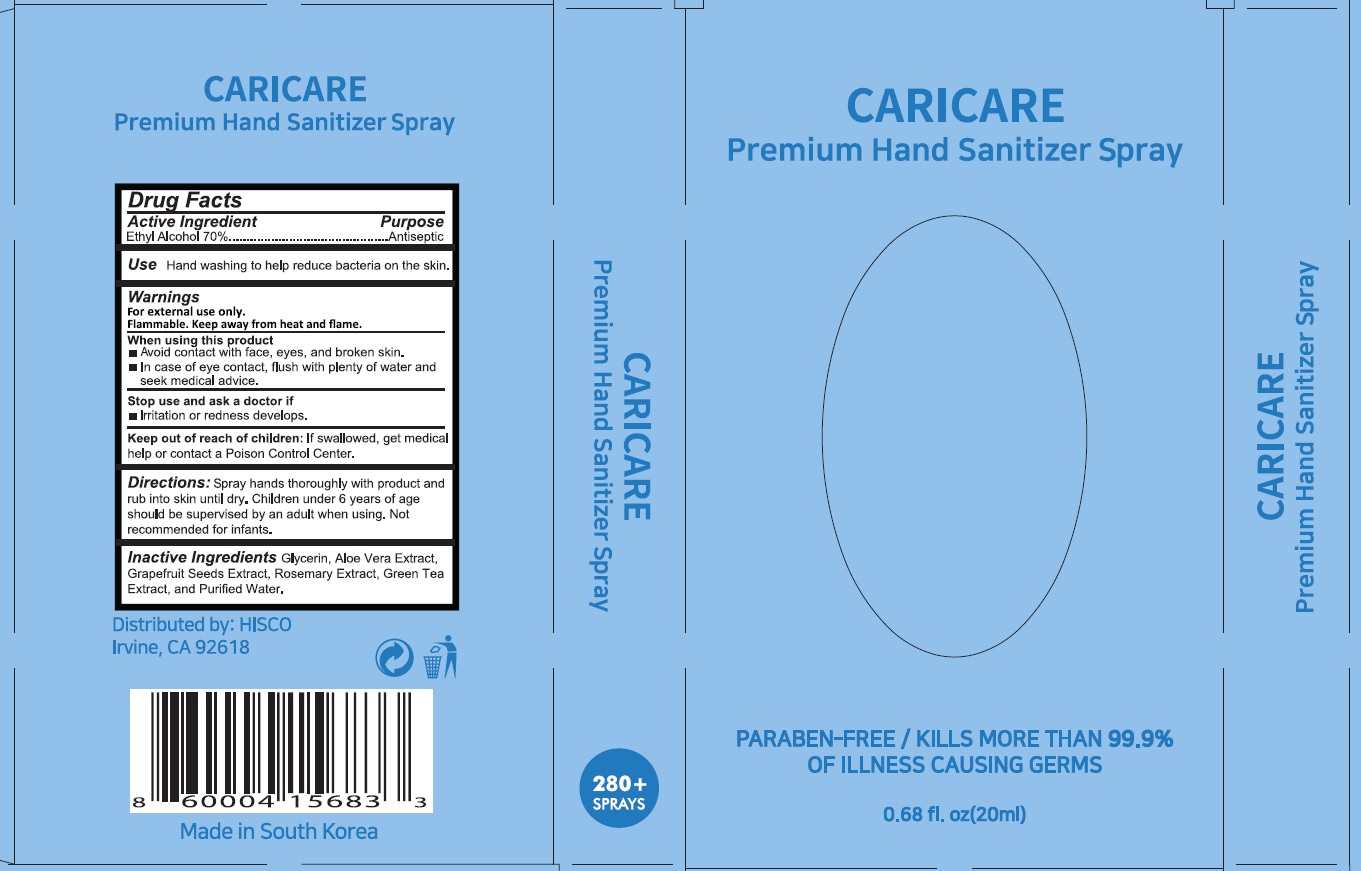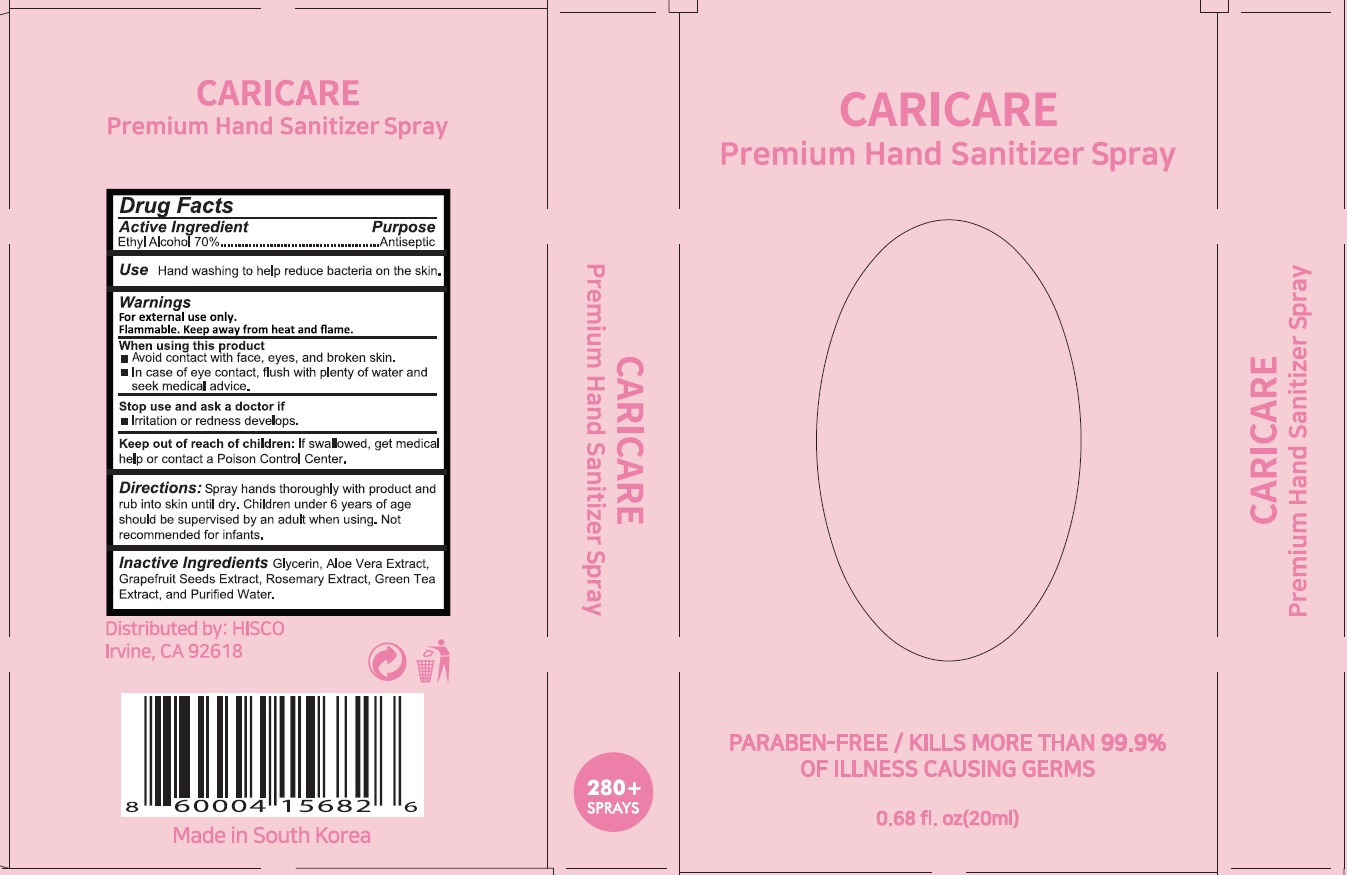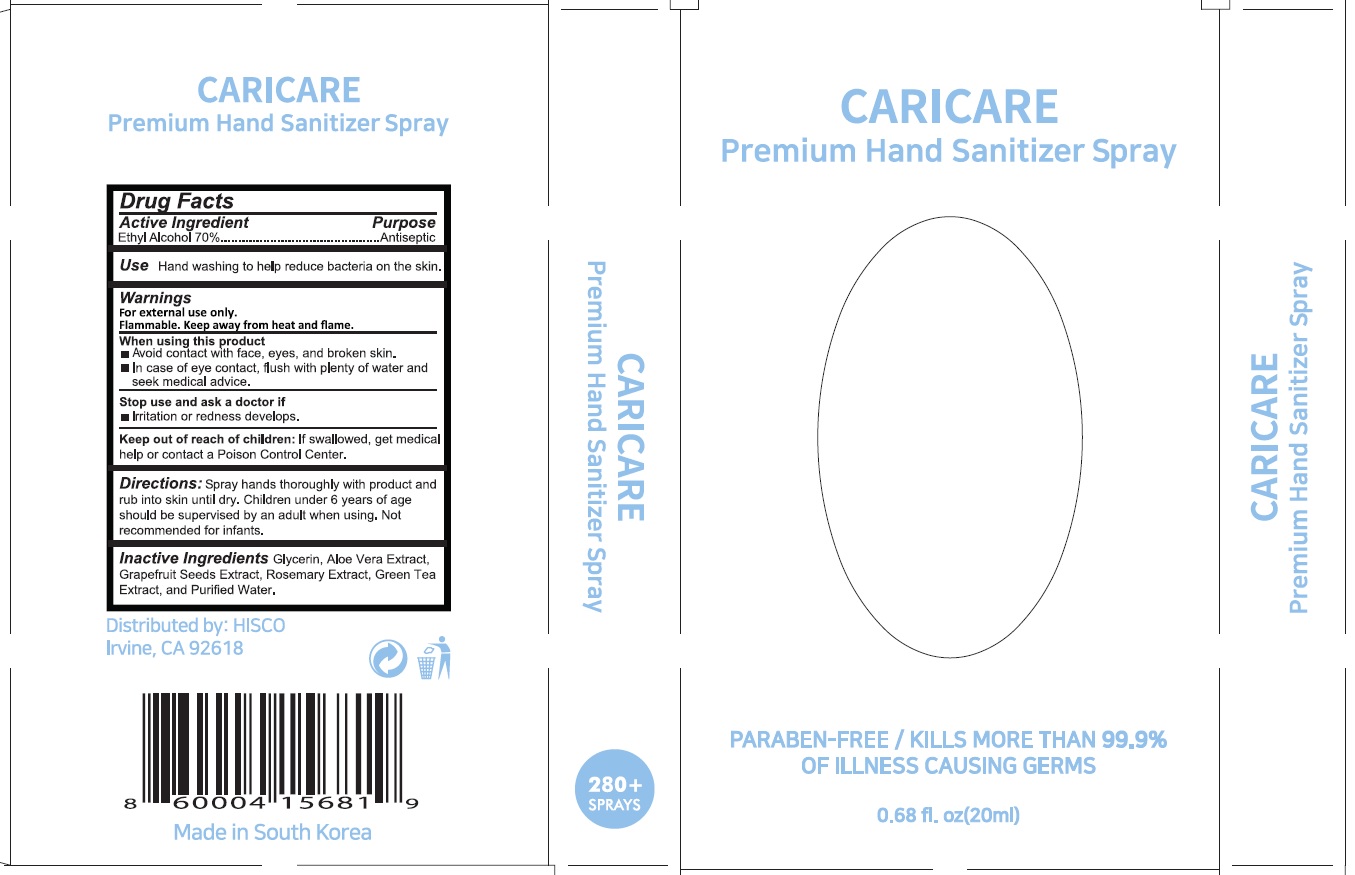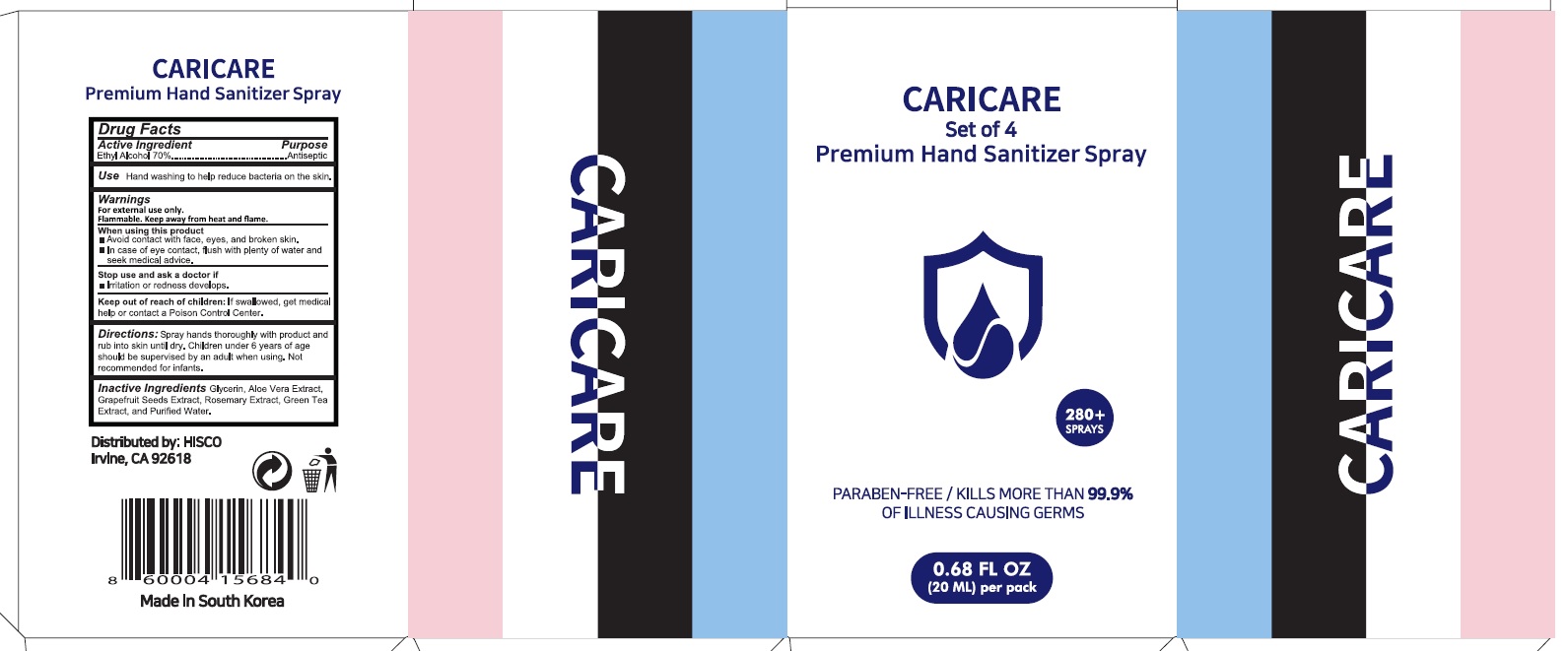 DRUG LABEL: CARRICARE Premium Hand Sanitizer
NDC: 74923-110 | Form: SPRAY
Manufacturer: THE SUN CO.LTD
Category: otc | Type: HUMAN OTC DRUG LABEL
Date: 20200604

ACTIVE INGREDIENTS: Alcohol 14 mL/20 mL
INACTIVE INGREDIENTS: Water; Glycerin; ALOE VERA LEAF; CITRUS PARADISI SEED; GREEN TEA LEAF

ACTIVE INGREDIENT

Ethyl Alcohol 70.0%

INACTIVE INGREDIENTS

Glycerin, Aloe Vera Extract, Grapefruit Seeds Extract, Rosemary Extract, Green Tea Extract, and Purified Water.

PURPOSE

Antiseptic

WARNINGS

For external use only

Flammable. Keep away from heat and flame.

When using this product
■ Avoid contact with face, eyes, and broken skin.
■ In case of eyes contact, flush with plenty of water and seek medical advice.

Stop use and ask a doctor if
■ irritation or redness develops.

KEEP OUT OF REACH OF CHILDREN

If swallowed, get medical help or contact a Poison Control Center.

Uses

■ Hand washing to help reduce bacteria on the skin.

Directions

■ Spray hands thoroughly with product and rub in to skin until dry.
■ Children under 6 years of age should be supervised by an adult when using.
■ Not recommended for infants.